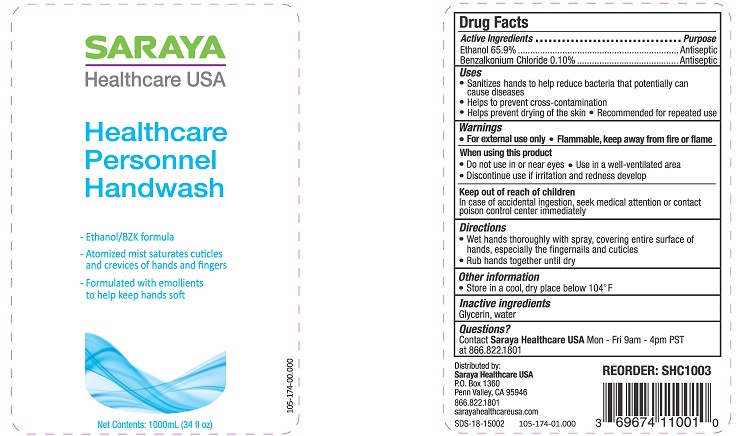 DRUG LABEL: Healthcare Personnel Handwash
NDC: 69674-110 | Form: LIQUID
Manufacturer: Saraya Healthcare
Category: otc | Type: HUMAN OTC DRUG LABEL
Date: 20190102

ACTIVE INGREDIENTS: BENZALKONIUM CHLORIDE 0.1 mg/100 mL; ALCOHOL 65.9 mL/100 mL
INACTIVE INGREDIENTS: WATER; GLYCERIN

SARAYA HEALTHCARE PERSONNEL HANDWASH

Active Ingredients

Ethanol 65.9%

Benzalkonium Chloride 0.10%

Purpose

Antiseptic

Antiseptic

Uses

- Sterilizes hands to help reduce bacteria that accidentally can cause diseases
- Helps to prevent cross-contamination
- Helps prevent drying of the skin
- Recommended for repeated use

Warnings

- For external use only
- Flammable, keep away from fire or flame

When using this product

- Do not use in or near eyes
- Use in a well-ventilated area
- Discontinue use if irritation and redness develop

Keep out of reach of children

In case of accidental ingestion, seek medical attention or contact a poison control center immediately

Directions

- Wet hands thoroughly with spray, covering entire surface of hands, especially the fingernails and cuticles
- Rub hands together until dry

Other information

- Store in a cool, dry place below 104°F

Inactive ingredients

Glycerin, water

Questions?

Contact Saraya Healthcare USA Mon - Fri 9am-4pm PST at 866.822.1801

Distributed by:

Saraya Healthcare USA

P.O. Box 1360

Penn Valley, CA 95946

866.822.1801

sarayahealthcareusa.com

SARAYA Healthcare USA

Healthcare Personnel Handwash

– Ethanol/BZK formula

– Atomized mist saturates cuticles and crevices of hands and fingers

– Formulated with emollients to help keep hands soft

Net Contents: 1000mL (34 fl oz)